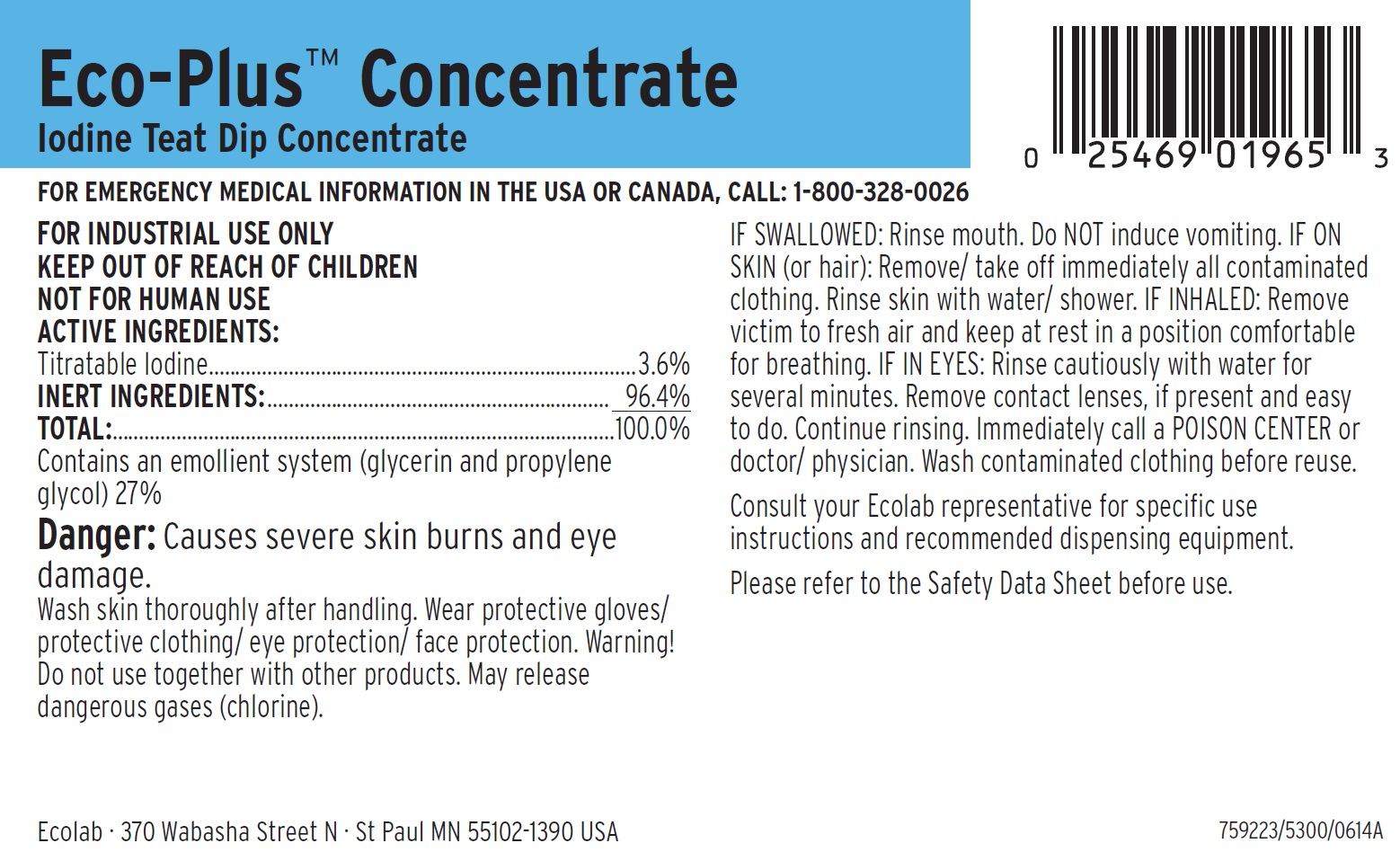 DRUG LABEL: Eco-Plus Concentrate
NDC: 47593-434 | Form: SOLUTION
Manufacturer: Ecolab Inc.
Category: animal | Type: OTC ANIMAL DRUG LABEL
Date: 20251012

ACTIVE INGREDIENTS: IODINE 36 mg/1 mL
INACTIVE INGREDIENTS: GLYCERIN; PROPYLENE GLYCOL

SAFE HANDLING WARNING

FOR INDUSTRIAL USE ONLY

KEEP OUT OF REACH OF CHILDREN

NOT FOR HUMAN USE

Danger: Causes severe skin burns and eye damage.

Wash skin thoroughly after handling. Wear protective gloves/ protective clothing/ eye protection/ face protection. Warning! Do not use together with other products. May release dangerous gases (chlorine).

OTHER SAFETY INFORMATION

IF SWALLOWED: Rinse mouth. Do NOT induce vomiting. IF ON SKIN (or hair): Remove/ take off immediately all contaminated clothing. Rinse skin with water/ shower. IF INHALED: Remove victim to fresh air and keep at rest in a position comfortable for breathing. IF IN EYES: Rinse cautiously with water for several minutes. Remove contact lenses, if present and easy to do. Continue rinsing. Immediately call a POISON CENTER or doctor/ physician. Wash contaminated clothing before reuse.

Consult your Ecolab representative for specific use instructions and recommended dispensing equipment.

Please refer to the Safety Data Sheet before use.

FOR EMERGENCY MEDICAL INFORMATION IN THE USA OR CANADA, CALL: 1-800-328-0026

Representative label and principal display panel

Eco-Plus™ Concentrate

Iodine Teat Dip Concentrate

ACTIVE INGREDIENTS:

Titratable Iodine ................................................................................3.6%

INERT INGREDIENTS: ................................................................ 96.4%

TOTAL:..............................................................................................100.0%

Contains an emollient system (glycerin and propylene glycol) 27%

Ecolab · 370 Wabasha Street N · St Paul MN 55102-1390 USA

759223/5300/0614A